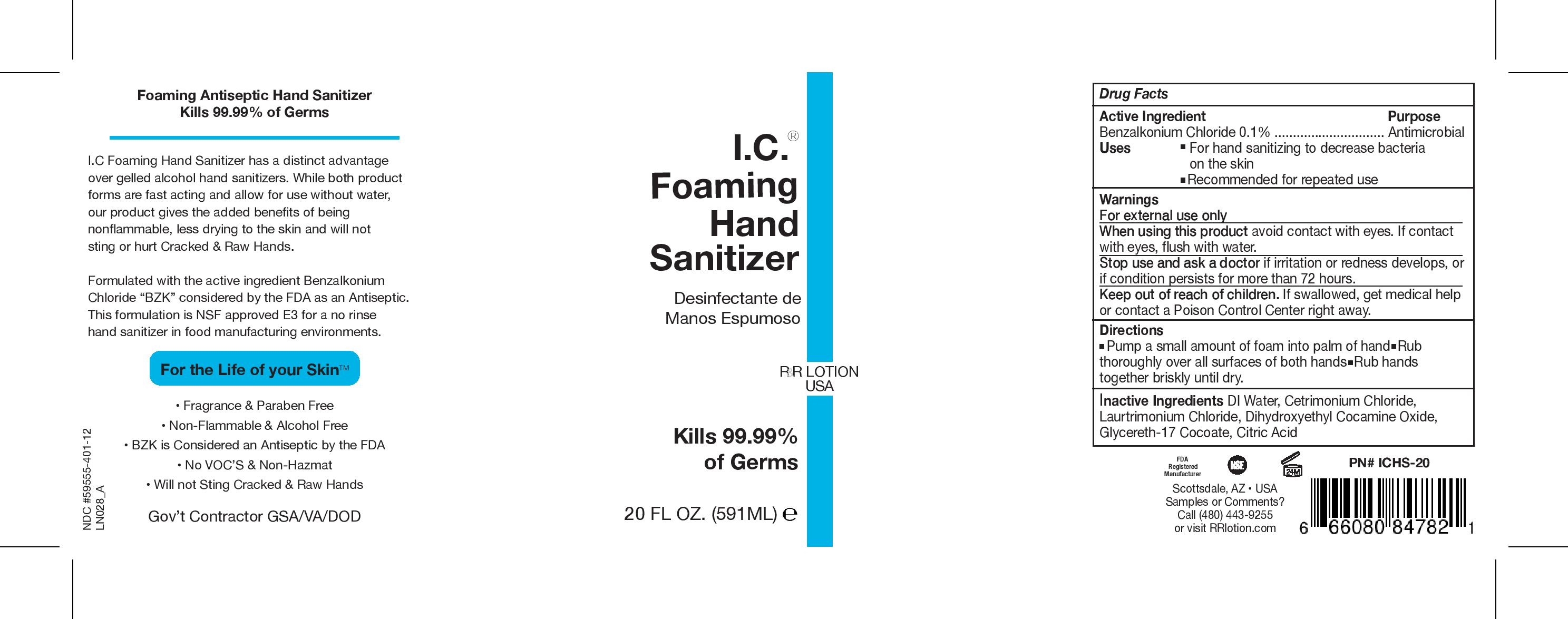 DRUG LABEL: I.C. Hand Sanitizer
NDC: 59555-401 | Form: AEROSOL, FOAM
Manufacturer: R&R Lotion, Inc.
Category: otc | Type: HUMAN OTC DRUG LABEL
Date: 20251216

ACTIVE INGREDIENTS: BENZALKONIUM CHLORIDE 1 mg/1 mL
INACTIVE INGREDIENTS: WATER; CETRIMONIUM CHLORIDE; LAURTRIMONIUM CHLORIDE; DIHYDROXYETHYL COCAMINE OXIDE; GLYCERETH-17 COCOATE; CITRIC ACID MONOHYDRATE

I.C. Hand Sanitizer

Drug Facts

Active Ingredient

Benzalkonium Chloride 0.1%

Purpose

Antimicrobial

Uses

- For hand sanitizing to decrease bacteria on the skin
- Recommended for repeated use

Warnings

For external use only

WHEN USING

When using this productavoid contact with eyes. If contact with eyes, flush with water.

Stop use and ask a doctorif irritation or redness develops, or if condition persists for more than 72 hours.

Keep out of reach of children.If swallowed, get medical help or contact a Poison Control Center right away.

Directions

- Pump a small amount of foam into palm of hand
- Rub thoroughly over all surfaces of both hands
- Rub hands together briskly until dry.

Inactive Ingredients

DI Water, Cetrimonium Chloride, Laurtrimonium Chloride, Dihydroxyethyl Cocamine Oxide, Glycereth-17 Cocoate, Citric Acid

Samples or Comments?

Call (480) 443-9255 or visit RRlotion.com

PRINCIPAL DISPLAY PANEL - 591 ML Bottle Label

I.C.®
Foaming
Hand
Sanitizer

R&R LOTION
USA

Kills 99.99%
of Germs

20 FL OZ. (591ML) ℮